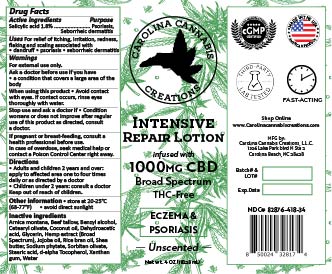 DRUG LABEL: Earthmed FS Psoriasis relief
NDC: 82876-994 | Form: LOTION
Manufacturer: Earthmed LLC
Category: otc | Type: HUMAN OTC DRUG LABEL
Date: 20250805

ACTIVE INGREDIENTS: SALICYLIC ACID 2.15 g/113.345 g
INACTIVE INGREDIENTS: .DELTA.9-TETRAHYDROCANNABINOLIC ACID 0.057 g/113.345 g; ARNICA MONTANA FLOWER WATER 1.15 g/113.345 g; DEHYDROACETIC ACID 0.088 g/113.345 g; COCONUT OIL 3.4 g/113.345 g; BEEF TALLOW 4.53 g/113.345 g; TOCOPHEROL 0.5 g/113.345 g; STEARIC ACID 0.57 g/113.345 g; XANTHAN GUM 0.57 g/113.345 g; GLYCERIN 4.53 g/113.345 g; CANNABIDIOL 1.13 g/113.345 g; WATER 85.648 g/113.345 g; SHEA BUTTER 3.4 g/113.345 g; RICE BRAN OIL 2.29 g/113.345 g; JOJOBA OIL 1.13 g/113.345 g; BENZYL ALCOHOL 0.935 g/113.345 g; SODIUM PHYTATE 0.125 g/113.345 g; CETEARYL OLIVATE 2.712 g/113.345 g; SORBITAN OLIVATE 1.808 g/113.345 g

Earthmed FS Psoriasis lotion

active ingredients

salicylic acid 1.8%

purpose

Topical analgesic

Skin protectant

Psoriasis

Uses

Temporary relief of skin irritation, itching redness and flaking associated with, eczema, psoriasis, seborrheic dermatitis, bug bites.

Warnings

For external use only

when using this product

avoid contact with eyes, avoid using on deep wounds, if you are allergic to any of the listed ingredients

Stop use and ask doctor if

condition worsens, symptoms last for more than 7 days, condition clears up but occurs again within a few days.

stop using and ask doctor if

condition worsens, symptoms last for more than 7 days, condition clears up but occurs again within a few days.

If pregnant or breast feeding

consult a health professional before use.

in case of overdose

seek medical help or contact a poison control center right away

Directions

Adults and children 12 years and over; apply to affected area one to four times daily.

children under 12 years; consult a doctor

keep out of reach of children

other information

store at 68-77 degrees F (20-20 degrees C), avoid direct sunlight

inactive ingredients

water(aqua), vitellaria paradoxa (shea) butter, cera alba (beeswax), oryza sativa (rice bran) oil, prunus dolcis (sweet almond) oil, simmondsia chinensis (jojoba) oil, cannabidiol, cannabis sativa (hemp seed) oil, maranta arundinacea (arrowroot) powder, benzyl alcohol, bonzoic acid, dehydroacetic acid, cymbopogon citratus (lemon grass) oil, melaleuca alternifolia (tea tree) oil, arnica montana, Eucalyptus oil.